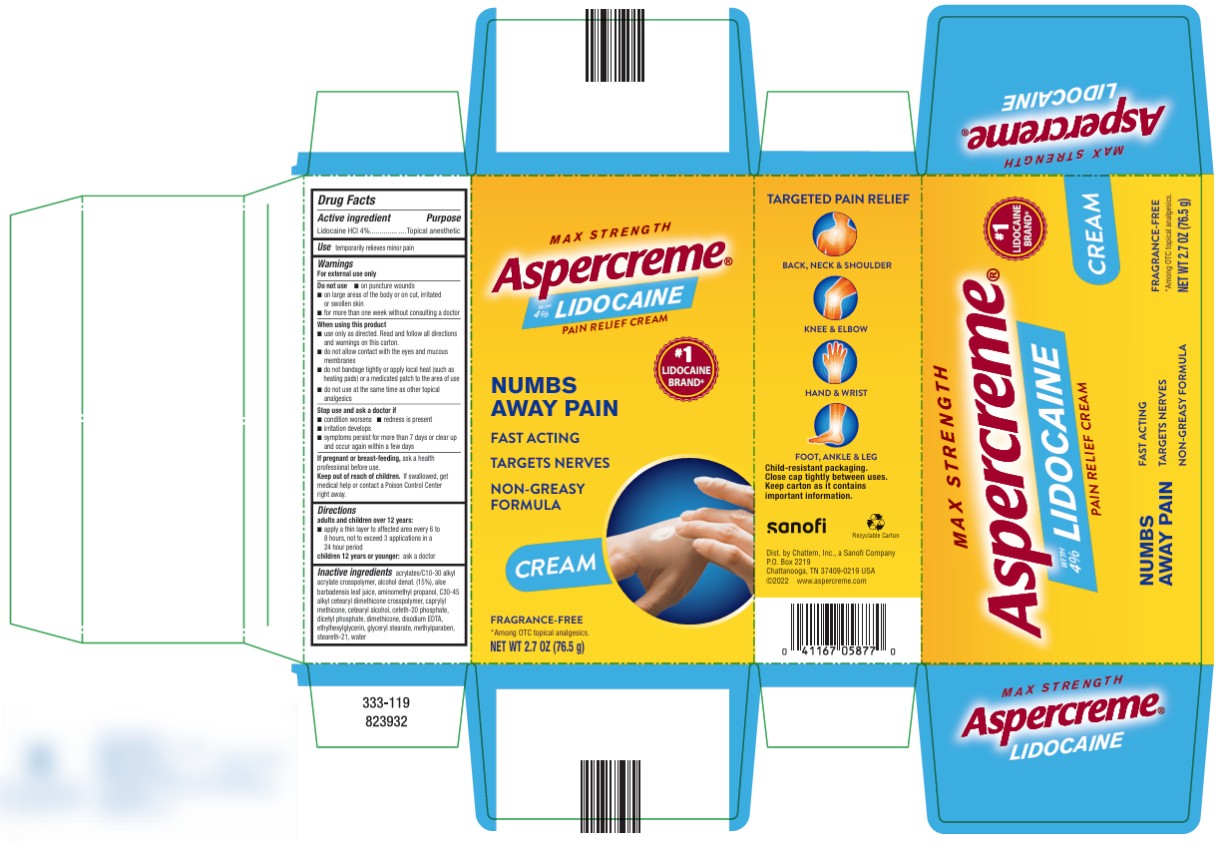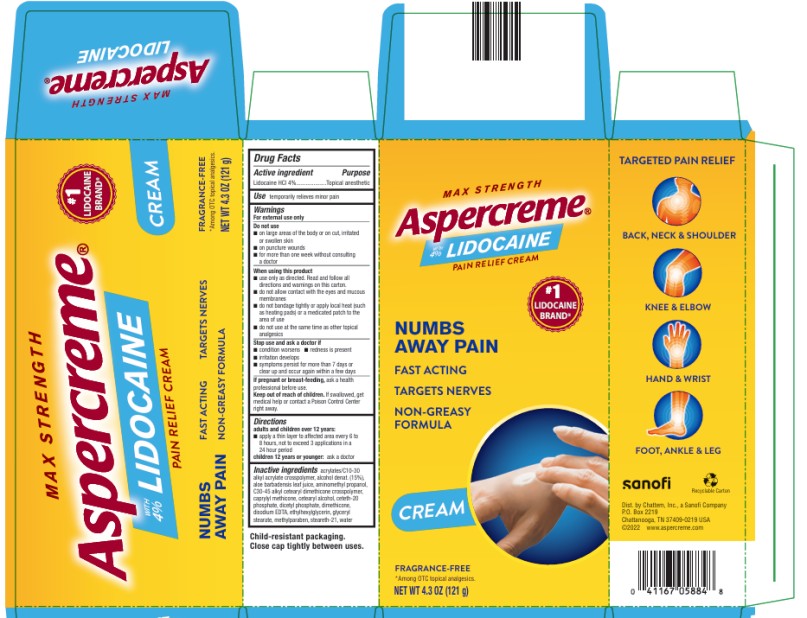 DRUG LABEL: Aspercreme with Lidocaine Pain Relieving Creme
NDC: 41167-0582 | Form: LOTION
Manufacturer: Chattem, Inc.
Category: otc | Type: HUMAN OTC DRUG LABEL
Date: 20240501

ACTIVE INGREDIENTS: LIDOCAINE HYDROCHLORIDE 4 g/100 g
INACTIVE INGREDIENTS: ALOE VERA LEAF; AMINOMETHYLPROPANOL; C30-45 ALKYL CETEARYL DIMETHICONE CROSSPOLYMER; CAPRYLYL TRISILOXANE; CETOSTEARYL ALCOHOL; CETETH-20 PHOSPHATE; DIHEXADECYL PHOSPHATE; DIMETHICONE; EDETATE DISODIUM; ETHYLHEXYLGLYCERIN; GLYCERYL MONOSTEARATE; METHYLPARABEN; STEARETH-21; WATER; ACRYLATES/C10-30 ALKYL ACRYLATE CROSSPOLYMER (60000 MPA.S AT 1.0%); ALCOHOL

Aspercreme with Lidocaine Pain Relieving Creme

Drug Facts

Active ingredient

Lidocaine HCI 4%

Purpose

Topical anesthetic

Uses

temporarily relieves minor pain

Warnings

For external use only

Do not use

- on puncture wounds
- on large areas of the body or on cut, irritated or swollen skin
- for more than one week without consulting a doctor

When using this product

- use only as directed. Read and follow all directions and warnings on this carton.
- do not allow contact with the eyes and mucous membranes
- do not bandage or apply local heat (such as heating pads) to the area of use
- do not use at the same time as other topical analgesics

Stop use and ask a doctor if

- condition worsens
- redness is present
- irritation develops
- symptoms persist for more than 7 days or clear up and occur again within a few days

If pregnant or breast-feeding,

ask a health professional before use.

Keep out of reach of children and pets.

If swallowed, get medical help or contact a Poison Control Center right away.

Directions

adults and children over 12 years:

- apply a thin layer to affected area every 6 to 8 hours, not to exceed 3 applications in a 24 hour period

children 12 years and younger: ask a doctor

Inactive ingredients

acrylates/C10-30 alkyl acrylate crosspolymer, alcohol denat. (15%), aloe barbadensis leaf juice, aminomethyl propanol, C30-45 alkyl cetearyl dimethicone crosspolymer, caprylyl methicone, cetearyl alcohol, ceteth-20 phosphate, dicetyl phosphate, dimethicone, disodium EDTA, ethylhexylglycerin, glyceryl stearate, methylparaben, steareth-21, water

PRINCIPAL DISPLAY PANEL

ODOR FREE
Aspercreme
WITH 4% LIDOCAINE
MAXIMUM STRENGTH
Pain Relieving CREME
Net wt 2.7 oz (76.5 g)

PRINCIPAL DISPLAY PANEL

ODOR FREE
Aspercreme
WITH 4% LIDOCAINE
MAXIMUM STRENGTH
Pain Relieving CREME
Net wt 4.3 oz (121 g)